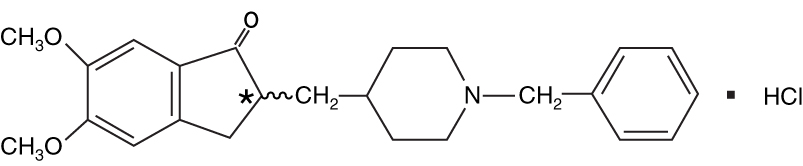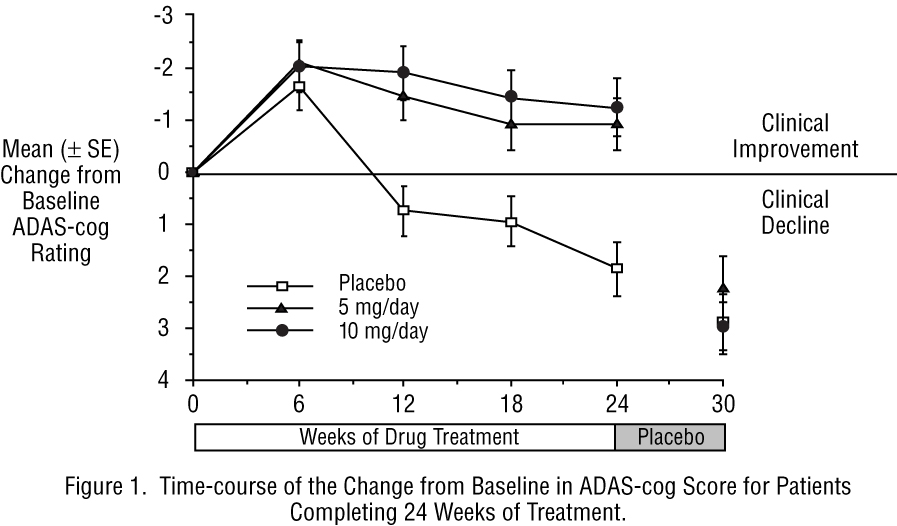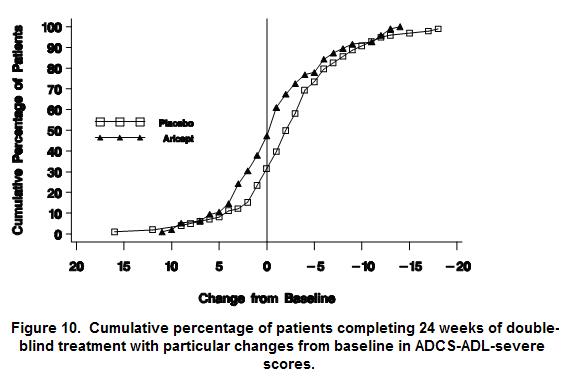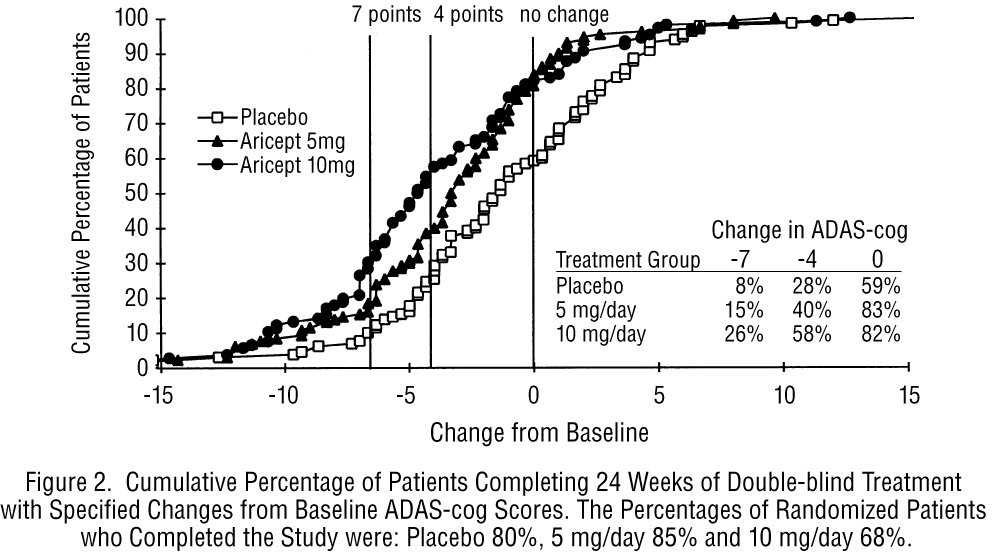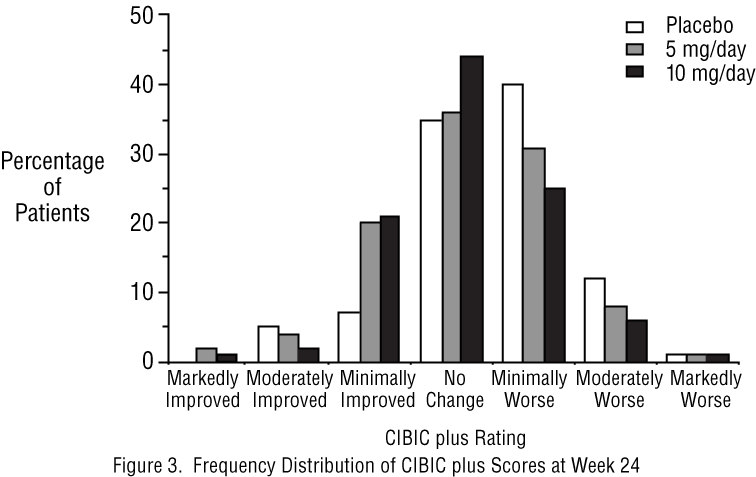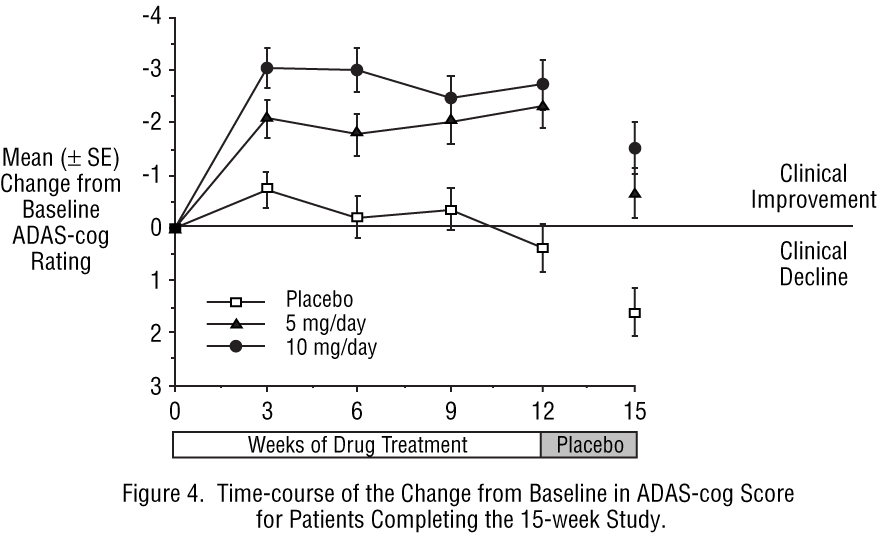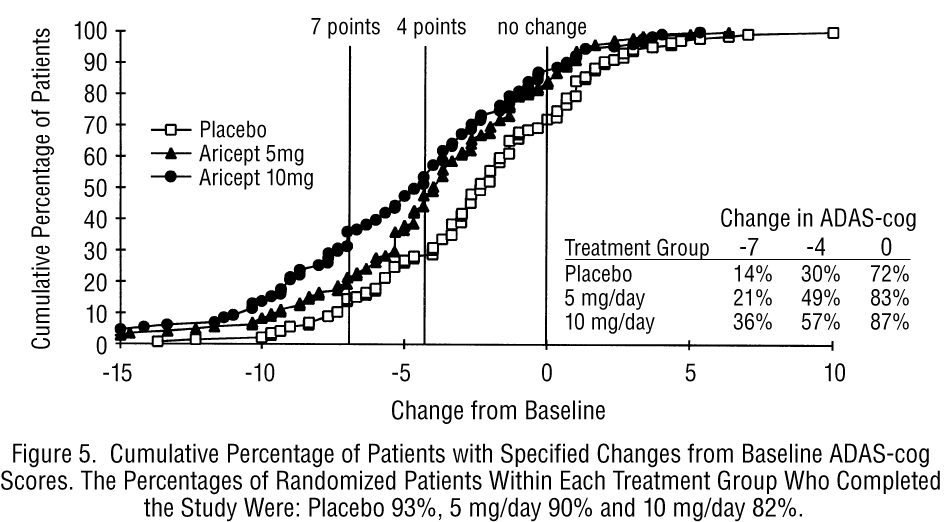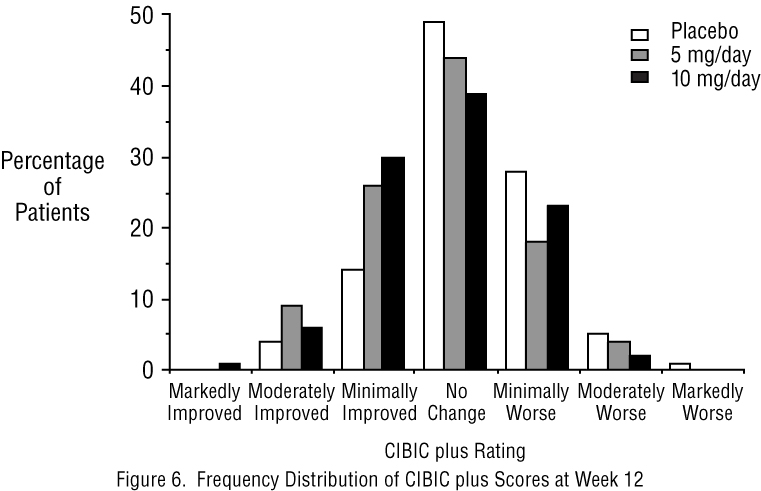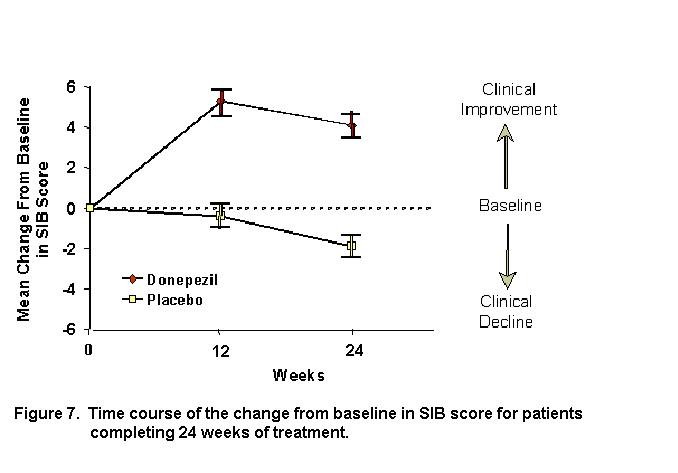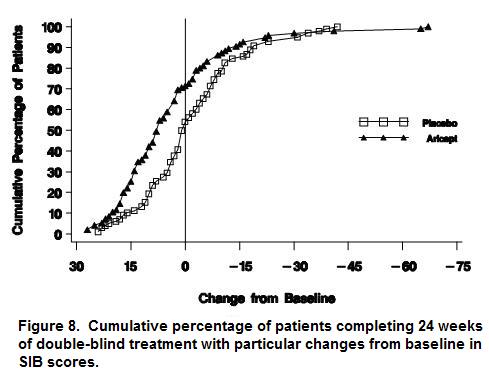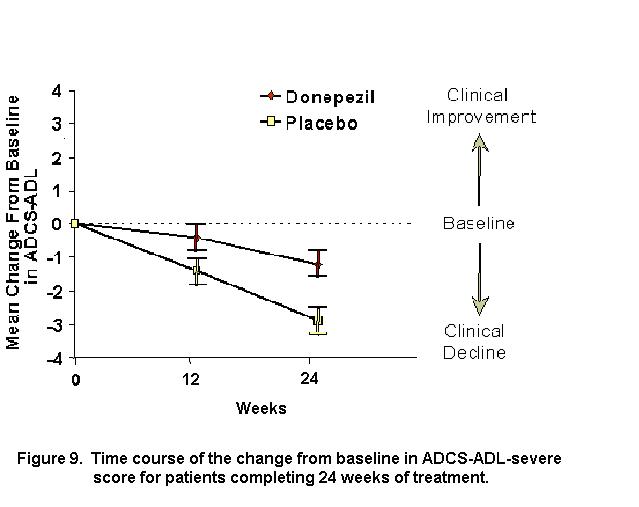 DRUG LABEL: Unknown
Manufacturer: Eisai Inc.
Category: prescription | Type: HUMAN PRESCRIPTION DRUG LABEL
Date: 20070524

ARICEPT® Oral Solution
(Donepezil Hydrochloride)

DESCRIPTION

ARICEPT® (donepezil hydrochloride) is a reversible inhibitor of the enzyme acetylcholinesterase, known chemically as (±)-2,3-dihydro-5,6-dimethoxy-2-[[1-(phenylmethyl)-4-piperidinyl]methyl]-1H-inden-1-one hydrochloride. Donepezil hydrochloride is commonly referred to in the pharmacological literature as E2020. It has an empirical formula of C24H29NO3HCl and a molecular weight of 415.96. Donepezil hydrochloride is a white crystalline powder and is freely soluble in chloroform, soluble in water and in glacial acetic acid, slightly soluble in ethanol and in acetonitrile and practically insoluble in ethyl acetate and in n-hexane.

Each 1mL of ARICEPT® Oral Solution contains 1 mg of donepezil hydrochloride. ARICEPT® Oral Solution also contains sorbitol solution 70%, povidone K-30, citric acid anhydrous, sodium citrate dihydrate, sodium benzoate, methylparaben, propylene glycol, sodium metabisulfite, purified water and strawberry flavor.

CLINICAL PHARMACOLOGY

Current theories on the pathogenesis of the cognitive signs and symptoms of Alzheimer's Disease attribute some of them to a deficiency of cholinergic neurotransmission. Donepezil hydrochloride is postulated to exert its therapeutic effect by enhancing cholinergic function. This is accomplished by increasing the concentration of acetylcholine through reversible inhibition of its hydrolysis by acetylcholinesterase. There is no evidence that donepezil alters the course of the underlying dementing process.

Clinical Trial Data

The effectiveness of ARICEPT® as a treatment for Alzheimer's Disease is demonstrated by the results of randomized, double-blind, placebo-controlled clinical investigations in mild, moderate and severe patients with Alzheimer's Disease.

Mild-Moderate Alzheimer's Disease

The effectiveness of ARICEPT® as a treatment for Alzheimer's Disease is demonstrated by the results of two randomized, double-blind, placebo-controlled clinical investigations in patients with Alzheimer's Disease (diagnosed by NINCDS and DSM III-R criteria, Mini-Mental State Examination ≥ 10 and ≤ 26 and Clinical Dementia Rating of 1 or 2). The mean age of patients participating in ARICEPT® trials was 73 years with a range of 50 to 94. Approximately 62% of patients were women and 38% were men. The racial distribution was white 95%, black 3% and other races 2%.

Study Outcome Measures

In each study, the effectiveness of treatment with ARICEPT® was evaluated using a dual outcome assessment strategy.

The ability of ARICEPT® to improve cognitive performance was assessed with the cognitive subscale of the Alzheimer's Disease Assessment Scale (ADAS-cog), a multi-item instrument that has been extensively validated in longitudinal cohorts of Alzheimer's Disease patients. The ADAS-cog examines selected aspects of cognitive performance including elements of memory, orientation, attention, reasoning, language and praxis. The ADAS-cog scoring range is from 0 to 70, with higher scores indicating greater cognitive impairment. Elderly normal adults may score as low as 0 or 1, but it is not unusual for non-demented adults to score slightly higher.

The patients recruited as participants in each study had mean scores on the Alzheimer's Disease Assessment Scale (ADAS-cog) of approximately 26 units, with a range from 4 to 61. Experience gained in longitudinal studies of ambulatory patients with mild to moderate Alzheimer's Disease suggest that they gain 6 to 12 units a year on the ADAS-cog. However, lesser degrees of change are seen in patients with very mild or very advanced disease because the ADAS-cog is not uniformly sensitive to change over the course of the disease. The annualized rate of decline in the placebo patients participating in ARICEPT® trials was approximately 2 to 4 units per year.

The ability of ARICEPT® to produce an overall clinical effect was assessed using a Clinician's Interview Based Impression of Change that required the use of caregiver information, the CIBIC plus. The CIBIC plus is not a single instrument and is not a standardized instrument like the ADAS-cog. Clinical trials for investigational drugs have used a variety of CIBIC formats, each different in terms of depth and structure.

As such, results from a CIBIC plus reflect clinical experience from the trial or trials in which it was used and cannot be compared directly with the results of CIBIC plus evaluations from other clinical trials. The CIBIC plus used in ARICEPT® trials was a semi-structured instrument that was intended to examine four major areas of patient function: General, Cognitive, Behavioral and Activities of Daily Living. It represents the assessment of a skilled clinician based upon his/her observations at an interview with the patient, in combination with information supplied by a caregiver familiar with the behavior of the patient over the interval rated. The CIBIC plus is scored as a seven point categorical rating, ranging from a score of 1, indicating "markedly improved," to a score of 4, indicating "no change" to a score of 7, indicating "markedly worse." The CIBIC plus has not been systematically compared directly to assessments not using information from caregivers (CIBIC) or other global methods.

Thirty-Week Study

In a study of 30 weeks duration, 473 patients were randomized to receive single daily doses of placebo, 5 mg/day or 10 mg/day of ARICEPT®. The 30-week study was divided into a 24-week double-blind active treatment phase followed by a 6-week single-blind placebo washout period. The study was designed to compare 5 mg/day or 10 mg/day fixed doses of ARICEPT® to placebo. However, to reduce the likelihood of cholinergic effects, the 10 mg/day treatment was started following an initial 7-day treatment with 5 mg/day doses.

Effects on the ADAS-cog

Figure 1 illustrates the time course for the change from baseline in ADAS-cog scores for all three dose groups over the 30 weeks of the study. After 24 weeks of treatment, the mean differences in the ADAS-cog change scores for ARICEPT® treated patients compared to the patients on placebo were 2.8 and 3.1 units for the 5 mg/day and 10 mg/day treatments, respectively. These differences were statistically significant. While the treatment effect size may appear to be slightly greater for the 10 mg/day treatment, there was no statistically significant difference between the two active treatments.

Following 6 weeks of placebo washout, scores on the ADAS-cog for both the ARICEPT® treatment groups were indistinguishable from those patients who had received only placebo for 30 weeks. This suggests that the beneficial effects of ARICEPT® abate over 6 weeks following discontinuation of treatment and do not represent a change in the underlying disease. There was no evidence of a rebound effect 6 weeks after abrupt discontinuation of therapy.

Figure 2 illustrates the cumulative percentages of patients from each of the three treatment groups who had attained the measure of improvement in ADAS-cog score shown on the X axis. Three change scores, (7-point and 4-point reductions from baseline or no change in score) have been identified for illustrative purposes and the percent of patients in each group achieving that result is shown in the inset table.

The curves demonstrate that both patients assigned to placebo and ARICEPT® have a wide range of responses, but that the active treatment groups are more likely to show the greater improvements. A curve for an effective treatment would be shifted to the left of the curve for placebo, while an ineffective or deleterious treatment would be superimposed upon or shifted to the right of the curve for placebo, respectively.

Effects on the CIBIC plus

Figure 3 is a histogram of the frequency distribution of CIBIC plus scores attained by patients assigned to each of the three treatment groups who completed 24 weeks of treatment. The mean drug-placebo differences for these groups of patients were 0.35 units and 0.39 units for 5 mg/day and 10 mg/day of ARICEPT®, respectively. These differences were statistically significant. There was no statistically significant difference between the two active treatments.

Fifteen-Week Study

In a study of 15 weeks duration, patients were randomized to receive single daily doses of placebo or either 5 mg/day or 10 mg/day of ARICEPT® for 12 weeks, followed by a 3-week placebo washout period. As in the 30-week study, to avoid acute cholinergic effects, the 10 mg/day treatment followed an initial 7-day treatment with 5 mg/day doses.

Effects on the ADAS-Cog

Figure 4 illustrates the time course of the change from baseline in ADAS-cog scores for all three dose groups over the 15 weeks of the study.

After 12 weeks of treatment, the differences in mean ADAS-cog change scores for the ARICEPT® treated patients compared to the patients on placebo were 2.7 and 3.0 units each, for the 5 and 10 mg/day ARICEPT®treatment groups respectively. These differences were statistically significant. The effect size for the 10 mg/day group may appear to be slightly larger than that for 5 mg/day. However, the differences between active treatments were not statistically significant.

Following 3 weeks of placebo washout, scores on the ADAS-cog for both the ARICEPT® treatment groups increased, indicating that discontinuation of ARICEPT® resulted in a loss of its treatment effect. The duration of this placebo washout period was not sufficient to characterize the rate of loss of the treatment effect, but, the 30-week study (see above) demonstrated that treatment effects associated with the use of ARICEPT® abate within 6 weeks of treatment discontinuation.

Figure 5 illustrates the cumulative percentages of patients from each of the three treatment groups who attained the measure of improvement in ADAS-cog score shown on the X axis. The same three change scores, (7-point and 4-point reductions from baseline or no change in score) as selected for the 30-week study have been used for this illustration. The percentages of patients achieving those results are shown in the inset table.

As observed in the 30-week study, the curves demonstrate that patients assigned to either placebo or to ARICEPT® have a wide range of responses, but that the ARICEPT® treated patients are more likely to show the greater improvements in cognitive performance.

Effects on the CIBIC plus

Figure 6 is a histogram of the frequency distribution of CIBIC plus scores attained by patients assigned to each of the three treatment groups who completed 12 weeks of treatment. The differences in mean scores for ARICEPT® treated patients compared to the patients on placebo at Week 12 were 0.36 and 0.38 units for the 5 mg/day and 10 mg/day treatment groups, respectively. These differences were statistically significant.

In both studies, patient age, sex and race were not found to predict the clinical outcome of ARICEPT® treatment.

Severe Alzheimer's Disease

Swedish 24-Week Study

The effectiveness of ARICEPT® as a treatment for severe Alzheimer's Disease is demonstrated by the results of a randomized, double-blind, placebo-controlled clinical study conducted in Sweden (24-Week Study) in patients with probable or possible Alzheimer's Disease diagnosed by NINCDS-ADRDA and DSM-IV criteria, MMSE: range of 1-10. Two hundred and forty eight (248) patients with severe Alzheimer's disease were randomized to ARICEPT® or placebo. For patients randomized to ARICEPT®, treatment was initiated at 5 mg once daily for 28-days and then increased to 10 mg once daily. At the end of the 24-week treatment period, 90.5% of the ARICEPT® -treated patients were receiving the 10 mg dose. The mean age of patients was 84.9 years with a range of 59 to 99. Approximately 77 % of patients were women and 23 % were men. Almost all patients were Caucasian. Probable AD was diagnosed in the majority of the patients (83.6% of ARICEPT®-treated patients and 84.2% of placebo-treated patients).

Study Outcome Measures

The effectiveness of treatment with ARICEPT® was determined using a dual outcome assessment strategy that evaluated cognitive function using an instrument designed for more impaired patients and overall function through caregiver-rated assessment. This study showed that patients on ARICEPT® experienced significant improvement on both measures compared to placebo.

The ability of ARICEPT® to improve cognitive performance was assessed with the Severe Impairment Battery (SIB). The SIB, a multi-item instrument, has been validated for the evaluation of cognitive function in patients with moderate to severe dementia. The SIB evaluates selective aspects of cognitive performance, including elements of memory, language, orientation, attention, praxis, visuospatial ability, construction, and social interaction. The SIB scoring range is from 0 to 100, with lower scores indicating greater cognitive impairment.

Daily function was assessed using the Modified Alzheimer's Disease Cooperative Study Activities of Daily Living Inventory for Severe Alzheimer's Disease (ADCS-ADL-severe). The ADCS-ADL-severe is derived from the Alzheimer's Disease Cooperative Study Activities of Daily Living Inventory, which is a comprehensive battery of ADL questions used to measure the functional capabilities of patients. Each ADL item is rated from the highest level of independent performance to complete loss. The ADCS-ADL-severe is a subset of 19 items, including ratings of the patient's ability to eat, dress, bathe, use the telephone, get around (or travel), and perform other activities of daily living; it has been validated for the assessment of patients with moderate to severe dementia. The ADCS-ADL-severe has a scoring range of 0 to 54 with the lower scores indicating greater functional impairment. The investigator performs the inventory by interviewing a caregiver, in this study a nurse staff member, familiar with the functioning of the patient.

Effects on the SIB

Figure 7 shows the time course for the change from baseline in SIB score for the two treatment groups over the 24 weeks of the study. At 24 weeks of treatment, the mean difference in the SIB change scores for ARICEPT® -treated patients compared to patients on placebo was 5.9 units. ARICEPT® treatment was statistically significantly superior to placebo.

Figure 8 illustrates the cumulative percentages of patients from each of the two treatment groups who attained the measure of improvement in SIB score shown on the X-axis. While patients assigned both to ARICEPT® and to placebo have a wide range of responses, the curves show that the ARICEPT® group is more likely to show a greater improvement in cognitive performance.

Effects on the ADCS-ADL-severe

Figure 9 illustrates the time course for the change from baseline in ADCS-ADL-severe scores for patients in the two treatment groups over the 24 weeks of the study. After 24 weeks of treatment, the mean difference in the ADCS-ADL-severe change scores for ARICEPT® treated patients compared to patients on placebo was 1.8 units. ARICEPT® treatment was statistically significantly superior to placebo.

Figure 10 shows the cumulative percentages of patients from each treatment group with specified changes from baseline ADCS-ADL-severe scores. While both patients assigned to ARICEPT®and placebo have a wide range of responses, the curves demonstrate that the ARICEPT®group is more likely to show a smaller decline or an improvement.

Japanese 24-Week Study

In a study of 24 weeks duration, conducted in Japan, 325 patients with severe Alzheimer's Disease were randomized to doses of 5 mg/day or 10 mg/day of donepezil, administered once daily, or placebo. Patients randomized to treatment with donepezil were to achieve their assigned doses by titration, beginning at 3 mg/day, and extending over a maximum of 6 weeks. 248 patients completed the study with similar proportions of patients completing the study in each treatment group. The primary efficacy measures for this study were the SIB and CIBIC plus.

At 24 weeks of treatment, statistically significant treatment differences were observed between the 10 mg/day dose of donepezil and placebo on both the SIB and CIBIC plus. The 5 mg/day dose of donepezil showed a statistically significant superiority to placebo on the SIB, but not on the CIBIC plus.

Clinical Pharmacokinetics

ARICEPT® Oral Solution is bioequivalent to ARICEPT® Tablets. Donepezil is well absorbed with a relative oral bioavailability of 100% and reaches peak plasma concentrations in 3 to 4 hours. Pharmacokinetics are linear over a dose range of 1-10 mg given once daily. Neither food nor time of administration (morning vs. evening dose) influences the rate or extent of absorption of ARICEPT® Tablets. Administration of ARICEPT® Oral Solution to healthy volunteers with a high-fat meal decreased Cmax by 17% and increased Tmax by 1 hour, while the AUC0-72 was similar under fed and fasted conditions. This delay in absorption and decrease in exposure is not likely to be clinically significant; therefore ARICEPT® Oral Solution can be taken without regard to meals.

The elimination half life of donepezil is about 70 hours and the mean apparent plasma clearance (Cl/F) is 0.13 L/hr/kg. Following multiple dose administration, donepezil accumulates in plasma by 4-7 fold and steady state is reached within 15 days. The steady state volume of distribution is 12 L/kg. Donepezil is approximately 96% bound to human plasma proteins, mainly to albumins (about 75%) and alpha1 - acid glycoprotein (about 21%) over the concentration range of 2-1000 ng/mL.

Donepezil is both excreted in the urine intact and extensively metabolized to four major metabolites, two of which are known to be active, and a number of minor metabolites, not all of which have been identified. Donepezil is metabolized by CYP 450 isoenzymes 2D6 and 3A4 and undergoes glucuronidation. Following administration of ^14C-labeled donepezil, plasma radioactivity, expressed as a percent of the administered dose, was present primarily as intact donepezil (53%) and as 6-O-desmethyl donepezil (11%), which has been reported to inhibit AChE to the same extent as donepezil in vitro and was found in plasma at concentrations equal to about 20% of donepezil. Approximately 57% and 15% of the total radioactivity was recovered in urine and feces, respectively, over a period of 10 days, while 28% remained unrecovered, with about 17% of the donepezil dose recovered in the urine as unchanged drug.

Special Populations

Hepatic Disease

In a study of 10 patients with stable alcoholic cirrhosis, the clearance of ARICEPT® was decreased by 20% relative to 10 healthy age and sex matched subjects.

Renal Disease

In a study of 4 patients with moderate to severe renal impairment (ClCr< 22 mL/min/1.73 m^2) the clearance of ARICEPT® did not differ from 4 age and sex matched healthy subjects.

Age

No formal pharmacokinetic study was conducted to examine age related differences in the pharmacokinetics of ARICEPT®. However, mean plasma ARICEPT® concentrations measured during therapeutic drug monitoring of elderly patients with Alzheimer's Disease are comparable to those observed in young healthy volunteers.

Gender and Race

No specific pharmacokinetic study was conducted to investigate the effects of gender and race on the disposition of ARICEPT®. However, retrospective pharmacokinetic analysis indicates that gender and race (Japanese and Caucasians) did not affect the clearance of ARICEPT®.

Drug-Drug Interactions

Drugs Highly Bound to Plasma Proteins

Drug displacement studies have been performed in vitro between this highly bound drug (96%) and other drugs such as furosemide, digoxin, and warfarin. ARICEPT® at concentrations of 0.3-10 μg/mL did not affect the binding of furosemide (5 μg/mL), digoxin (2 ng/mL), and warfarin (3 μg/mL) to human albumin. Similarly, the binding of ARICEPT® to human albumin was not affected by furosemide, digoxin and warfarin.

Effect of ARICEPT® on the Metabolism of Other Drugs

No in vivo clinical trials have investigated the effect of ARICEPT® on the clearance of drugs metabolized by CYP 3A4 (e.g. cisapride, terfenadine) or by CYP 2D6 (e.g. imipramine). However, in vitro studies show a low rate of binding to these enzymes (mean Ki about 50-130 μM), that, given the therapeutic plasma concentrations of donepezil (164 nM), indicates little likelihood of interference.

Whether ARICEPT® has any potential for enzyme induction is not known.

Formal pharmacokinetic studies evaluated the potential of ARICEPT® for interaction with theophylline, cimetidine, warfarin and digoxin. No significant effects on the pharmacokinetics of these drugs were observed.

Effect of Other Drugs on the Metabolism of ARICEPT®

Ketoconazole and quinidine, inhibitors of CYP450, 3A4 and 2D6, respectively, inhibit donepezil metabolism in vitro. Whether there is a clinical effect of quinidine is not known. In a 7-day crossover study in 18 healthy volunteers, ketoconazole (200mg q.d.) increased mean donepezil (5mg q.d.) concentrations (AUC0-24 and Cmax) by 36%. The clinical relevance of this increase in concentration is unknown.

Inducers of CYP 2D6 and CYP 3A4 (e.g., phenytoin, carbamazepine, dexamethasone, rifampin, and phenobarbital) could increase the rate of elimination of ARICEPT®.

Formal pharmacokinetic studies demonstrated that the metabolism of ARICEPT® is not significantly affected by concurrent administration of digoxin or cimetidine.

INDICATIONS AND USAGE

ARICEPT® is indicated for the treatment of dementia of the Alzheimer's type. Efficacy has been demonstrated in patients with mild to moderate Alzheimer's Disease, as well as in patients with severe Alzheimer's Disease.

CONTRAINDICATIONS

ARICEPT® is contraindicated in patients with known hypersensitivity to donepezil hydrochloride or to piperidine derivatives.

WARNINGS

Anesthesia

ARICEPT®, as a cholinesterase inhibitor, is likely to exaggerate succinylcholine-type muscle relaxation during anesthesia.

Cardiovascular Conditions

Because of their pharmacological action, cholinesterase inhibitors may have vagotonic effects on the sinoatrial and atrioventricular nodes. This effect may manifest as bradycardia or heart block in patients both with and without known underlying cardiac conduction abnormalities. Syncopal episodes have been reported in association with the use of ARICEPT®.

Gastrointestinal Conditions

Through their primary action, cholinesterase inhibitors may be expected to increase gastric acid secretion due to increased cholinergic activity. Therefore, patients should be monitored closely for symptoms of active or occult gastrointestinal bleeding, especially those at increased risk for developing ulcers, e.g., those with a history of ulcer disease or those receiving concurrent nonsteroidal anti-inflammatory drugs (NSAIDS). Clinical studies of ARICEPT® have shown no increase, relative to placebo, in the incidence of either peptic ulcer disease or gastrointestinal bleeding.

ARICEPT®, as a predictable consequence of its pharmacological properties, has been shown to produce diarrhea, nausea and vomiting. These effects, when they occur, appear more frequently with the 10 mg/day dose than with the 5 mg/day dose. In most cases, these effects have been mild and transient, sometimes lasting one to three weeks, and have resolved during continued use of ARICEPT®.

Genitourinary

Although not observed in clinical trials of ARICEPT®, cholinomimetics may cause bladder outflow obstruction.

Neurological Conditions

Seizures: Cholinomimetics are believed to have some potential to cause generalized convulsions. However, seizure activity also may be a manifestation of Alzheimer's Disease.

Pulmonary Conditions

Because of their cholinomimetic actions, cholinesterase inhibitors should be prescribed with care to patients with a history of asthma or obstructive pulmonary disease.

Sulfites

ARICEPT® Oral Solution contains sodium metabisulfite, a sulfite that may cause allergic-type reactions including anaphylactic symptoms and life-threatening or less severe asthmatic episodes in certain susceptible people. The overall prevalence of sulfite sensitivity in the general population is unknown and probably low. Sulfite sensitivity is seen more frequently in asthmatic than nonasthmatic people.

PRECAUTIONS

Drug-Drug Interactions

(see Clinical Pharmacology: Clinical Pharmacokinetics: Drug-drug Interactions)

Effect of ARICEPT® on the Metabolism of Other Drugs

No in vivo clinical trials have investigated the effect of ARICEPT® on the clearance of drugs metabolized by CYP 3A4 (e.g. cisapride, terfenadine) or by CYP 2D6 (e.g. imipramine). However, in vitro studies show a low rate of binding to these enzymes (mean Ki about 50-130 μM), that, given the therapeutic plasma concentrations of donepezil (164 nM), indicates little likelihood of interference.

Whether ARICEPT® has any potential for enzyme induction is not known.

Formal pharmacokinetic studies evaluated the potential of ARICEPT® for interaction with theophylline, cimetidine, warfarin and digoxin. No significant effects on the pharmacokinetics of these drugs were observed..

Effect of Other Drugs on the Metabolism of ARICEPT®

Ketoconazole and quinidine, inhibitors of CYP450, 3A4 and 2D6, respectively, inhibit donepezil metabolism in vitro. Whether there is a clinical effect of these inhibitors is not known. In a 7-day crossover study in 18 healthy volunteers, ketoconazole (200mg q.d.) increased mean donepezil (5mg q.d.) concentrations (AUC0-24 and Cmax) by 36%. The clinical relevance of this increase in concentration is unknown.

Inducers of CYP 2D6 and CYP 3A4 (e.g., phenytoin, carbamazepine, dexamethasone, rifampin, and phenobarbital) could increase the rate of elimination of ARICEPT®.

Formal pharmacokinetic studies demonstrated that the metabolism of ARICEPT® is not significantly affected by concurrent administration of digoxin or cimetidine.

Use with Anticholinergics

Because of their mechanism of action, cholinesterase inhibitors have the potential to interfere with the activity of anticholinergic medications.

Use with Cholinomimetics and Other Cholinesterase Inhibitors

A synergistic effect may be expected when cholinesterase inhibitors are given concurrently with succinylcholine, similar neuromuscular blocking agents or cholinergic agonists such as bethanechol.

Carcinogenesis, Mutagenesis, Impairment of Fertility

No evidence of a carcinogenic potential was obtained in an 88-week carcinogenicity study of donepezil hydrochloride conducted in CD-1 mice at doses up to 180 mg/kg/day (approximately 90 times the maximum recommended human dose on a mg/m^2 basis), or in a 104-week carcinogenicity study in Sprague-Dawley rats at doses up to 30mg/kg/day (approximately 30 times the maximum recommended human dose on a mg/m^2 basis).

Donepezil was not mutagenic in the Ames reverse mutation assay in bacteria, or in a mouse lymphoma forward mutation assay in vitro. In the chromosome aberration test in cultures of Chinese hamster lung (CHL) cells, some clastogenic effects were observed. Donepezil was not clastogenic in the in vivo mouse micronucleus test and was not genotoxic in an in vivo unscheduled DNA synthesis assay in rats.

Donepezil had no effect on fertility in rats at doses up to 10 mg/kg/day (approximately 8 times the maximum recommended human dose on a mg/m^2 basis).

Pregnancy

Pregnancy Category C

Teratology studies conducted in pregnant rats at doses up to 16 mg/kg/day (approximately 13 times the maximum recommended human dose on a mg/m^2 basis) and in pregnant rabbits at doses up to 10 mg/kg/day (approximately 16 times the maximum recommended human dose on a mg/m^2 basis) did not disclose any evidence for a teratogenic potential of donepezil. However, in a study in which pregnant rats were given up to 10 mg/kg/day (approximately 8 times the maximum recommended human dose on a mg/m^2 basis) from day 17 of gestation through day 20 postpartum, there was a slight increase in still births and a slight decrease in pup survival through day 4 postpartum at this dose; the next lower dose tested was 3 mg/kg/day. There are no adequate or well-controlled studies in pregnant women. ARICEPT® should be used during pregnancy only if the potential benefit justifies the potential risk to the fetus.

Nursing Mothers

It is not known whether donepezil is excreted in human breast milk. ARICEPT® has no indication for use in nursing mothers.

Pediatric Use

There are no adequate and well-controlled trials to document the safety and efficacy of ARICEPT® in any illness occurring in children.

Geriatric Use

Alzheimer's disease is a disorder occurring primarily in individuals over 55 years of age. The mean age of patients enrolled in the clinical studies with ARICEPT® was 73 years; 80% of these patients were between 65 and 84 years old and 49% of patients were at or above the age of 75. The efficacy and safety data presented in the clinical trials section were obtained from these patients. There were no clinically significant differences in most adverse events reported by patient groups ≥ 65 years old and < 65 years old.

ADVERSE REACTIONS

Mild to Moderate Alzheimer's Disease Trials

Adverse Events Leading to Discontinuation

The rates of discontinuation from controlled clinical trials of ARICEPT® due to adverse events for the ARICEPT® 5 mg/day treatment groups were comparable to those of placebo-treatment groups at approximately 5%. The rate of discontinuation of patients who received 7-day escalations from 5 mg/day to 10 mg/day, was higher at 13%.

The most common adverse events leading to discontinuation, defined as those occurring in at least 2% of patients and at twice the incidence seen in placebo patients, are shown in Table 1.

Table 1. Most Frequent Adverse Events Leading to Withdrawal from Controlled Clinical Trials by Dose Group
Dose Group | Placebo | 5 mg/day ARICEPT® | 10 mg/day ARICEPT®
Patients Randomized | 355 | 350 | 315
Event/%Discontinuing
Nausea | 1% | 1% | 3%
Diarrhea | 0% | <1% | 3%
Vomiting | <1% | <1% | 2%

Most Frequent Adverse Clinical Events Seen in Association with the Use of ARICEPT®

The most common adverse events, defined as those occurring at a frequency of at least 5% in patients receiving 10 mg/day and twice the placebo rate, are largely predicted by ARICEPT®'s cholinomimetic effects. These include nausea, diarrhea, insomnia, vomiting, muscle cramp, fatigue and anorexia. These adverse events were often of mild intensity and transient, resolving during continued ARICEPT® treatment without the need for dose modification.

There is evidence to suggest that the frequency of these common adverse events may be affected by the rate of titration. An open-label study was conducted with 269 patients who received placebo in the 15 and 30-week studies. These patients were titrated to a dose of 10 mg/day over a 6-week period. The rates of common adverse events were lower than those seen in patients titrated to 10 mg/day over one week in the controlled clinical trials and were comparable to those seen in patients on 5 mg/day.

See Table 2 for a comparison of the most common adverse events following one and six week titration regimens.

Table 2. Comparison of rates of adverse events in patients titrated to 10 mg/day over 1 and 6 weeks
 | No Titration |  | One week titration | Six week titration
Adverse Event | Placebo (n=315) | 5 mg/day (n=311) | 10 mg/day (n=315) | 10 mg/day (n=269)
Nausea | 6% | 5% | 19% | 6%
Diarrhea | 5% | 8% | 15% | 9%
Insomnia | 6% | 6% | 14% | 6%
Fatigue | 3% | 4% | 8% | 3%
Vomiting | 3% | 3% | 8% | 5%
Muscle cramps | 2% | 6% | 8% | 3%
Anorexia | 2% | 3% | 7% | 3%

Adverse Events Reported in Controlled Trials

The events cited reflect experience gained under closely monitored conditions of clinical trials in a highly selected patient population. In actual clinical practice or in other clinical trials, these frequency estimates may not apply, as the conditions of use, reporting behavior, and the kinds of patients treated may differ. Table 3 lists treatment emergent signs and symptoms that were reported in at least 2% of patients in placebo-controlled trials who received ARICEPT® and for which the rate of occurrence was greater for ARICEPT® assigned than placebo assigned patients. In general, adverse events occurred more frequently in female patients and with advancing age.

Table 3. Adverse Events Reported in Controlled Clinical Trials in at Least 2% of Patients Receiving ARICEPT® and at a Higher Frequency than Placebo-treated Patients
Body System/Adverse Event | Placebo (n=355) | ARICEPT® (n=747)
Percent of Patients with any Adverse Event | 72 | 74
Body as a Whole
Headache | 9 | 10
Pain, various locations | 8 | 9
Accident | 6 | 7
Fatigue | 3 | 5
Cardiovascular System
Syncope | 1 | 2
Digestive System
Nausea | 6 | 11
Diarrhea | 5 | 10
Vomiting | 3 | 5
Anorexia | 2 | 4
Hemic and Lymphatic System
Ecchymosis | 3 | 4
Metabolic and Nutritional Systems
Weight Decrease | 1 | 3
Musculoskeletal System
Muscle Cramps | 2 | 6
Arthritis | 1 | 2
Nervous System
Insomnia | 6 | 9
Dizziness | 6 | 8
Depression | <1 | 3
Abnormal Dreams | 0 | 3
Somnolence | <1 | 2
Urogenital System
Frequent Urination | 1 | 2

Other Adverse Events Observed During Clinical Trials

ARICEPT® has been administered to over 1700 individuals during clinical trials worldwide. Approximately 1200 of these patients have been treated for at least 3 months and more than 1000 patients have been treated for at least 6 months. Controlled and uncontrolled trials in the United States included approximately 900 patients. In regards to the highest dose of 10 mg/day, this population includes 650 patients treated for 3 months, 475 patients treated for 6 months and 116 patients treated for over 1 year. The range of patient exposure is from 1 to 1214 days.

Treatment emergent signs and symptoms that occurred during 3 controlled clinical trials and two open-label trials in the United States were recorded as adverse events by the clinical investigators using terminology of their own choosing. To provide an overall estimate of the proportion of individuals having similar types of events, the events were grouped into a smaller number of standardized categories using a modified COSTART dictionary and event frequencies were calculated across all studies. These categories are used in the listing below. The frequencies represent the proportion of 900 patients from these trials who experienced that event while receiving ARICEPT®. All adverse events occurring at least twice are included, except for those already listed in Tables 2 or 3, COSTART terms too general to be informative, or events less likely to be drug caused. Events are classified by body system and listed using the following definitions: frequent adverse events - those occurring in at least 1/100 patients; infrequent adverse events - those occurring in 1/100 to 1/1000 patients. These adverse events are not necessarily related to ARICEPT® treatment and in most cases were observed at a similar frequency in placebo-treated patients in the controlled studies. No important additional adverse events were seen in studies conducted outside the United States.

Body as a Whole:Frequent: influenza, chest pain, toothache; Infrequent: fever, edema face, periorbital edema, hernia hiatal, abscess, cellulitis, chills, generalized coldness, head fullness, listlessness.

Cardiovascular System:Frequent: hypertension, vasodilation, atrial fibrillation, hot flashes, hypotension; Infrequent: angina pectoris, postural hypotension, myocardial infarction, AV block (first degree), congestive heart failure, arteritis, bradycardia, peripheral vascular disease, supraventricular tachycardia, deep vein thrombosis.

Digestive System:Frequent: fecal incontinence, gastrointestinal bleeding, bloating, epigastric pain; Infrequent: eructation, gingivitis, increased appetite, flatulence, periodontal abscess, cholelithiasis, diverticulitis, drooling, dry mouth, fever sore, gastritis, irritable colon, tongue edema, epigastric distress, gastroenteritis, increased transaminases, hemorrhoids, ileus, increased thirst, jaundice, melena, polydipsia, duodenal ulcer, stomach ulcer.

Endocrine System:Infrequent: diabetes mellitus, goiter.

Hemic and Lymphatic System:Infrequent: anemia, thrombocythemia, thrombocytopenia, eosinophilia, erythrocytopenia.

Metabolic and Nutritional Disorders:Frequent: dehydration; Infrequent: gout, hypokalemia, increased creatine kinase, hyperglycemia, weight increase, increased lactate dehydrogenase.

Musculoskeletal System:Frequent: bone fracture; Infrequent: muscle weakness, muscle fasciculation.

Nervous System:Frequent: delusions, tremor, irritability, paresthesia, aggression, vertigo, ataxia, increased libido, restlessness, abnormal crying, nervousness, aphasia; Infrequent: cerebrovascular accident, intracranial hemorrhage, transient ischemic attack, emotional lability, neuralgia, coldness (localized), muscle spasm, dysphoria, gait abnormality, hypertonia, hypokinesia, neurodermatitis, numbness (localized), paranoia, dysarthria, dysphasia, hostility, decreased libido, melancholia, emotional withdrawal, nystagmus, pacing.

Respiratory System:Frequent: dyspnea, sore throat, bronchitis; Infrequent: epistaxis, post nasal drip, pneumonia, hyperventilation, pulmonary congestion, wheezing, hypoxia, pharyngitis, pleurisy, pulmonary collapse, sleep apnea, snoring.

Skin and Appendages:Frequent: pruritus, diaphoresis, urticaria; Infrequent: dermatitis, erythema, skin discoloration, hyperkeratosis, alopecia, fungal dermatitis, herpes zoster, hirsutism, skin striae, night sweats, skin ulcer.

Special Senses:Frequent: cataract, eye irritation, vision blurred; Infrequent: dry eyes, glaucoma, earache, tinnitus, blepharitis, decreased hearing, retinal hemorrhage, otitis externa, otitis media, bad taste, conjunctival hemorrhage, ear buzzing, motion sickness, spots before eyes.

Urogenital System:Frequent: urinary incontinence, nocturia; Infrequent: dysuria, hematuria, urinary urgency, metrorrhagia, cystitis, enuresis, prostate hypertrophy, pyelonephritis, inability to empty bladder, breast fibroadenosis, fibrocystic breast, mastitis, pyuria, renal failure, vaginitis.

Severe Alzheimer's Disease

Adverse Events Leading to Discontinuation

The rates of discontinuation from controlled clinical trials of ARICEPT® due to adverse events for the ARICEPT® patients were approximately 12% compared to 7% for placebo patients.

The most common adverse events leading to discontinuation, defined as those occurring in at least 2% of ARICEPT® patients and at twice the incidence seen in placebo patients, were anorexia (2% vs 1% placebo), nausea (2% vs <1% placebo), diarrhea (2% vs 0% placebo) and urinary tract infection (2% vs 1% placebo).

Most Frequent Adverse Clinical Events Seen in Association with the Use of ARICEPT®

The most common adverse events, defined as those occurring at a frequency of at least 5% in patients receiving ARICEPT® and twice the placebo rate, are largely predicted by ARICEPT®'s cholinomimetic effects. These include diarrhea, anorexia, vomiting, nausea, and ecchymosis. These adverse events were often of mild intensity and transient, resolving during continued ARICEPT® treatment without the need for dose modification.

Adverse Events Reported in Controlled Trials

Table 4 lists treatment emergent signs and symptoms that were reported in at least 2% of patients in placebo-controlled trials who received ARICEPT® and for which the rate of occurrence was greater for ARICEPT® assigned than placebo assigned patients.

Table 4. Adverse Events Reported in Controlled Clinical Trials in Severe Alzheimer's Disease in at Least 2% of Patients Receiving ARICEPT® and at a Higher Frequency than Placebo-treated Patients
Body System/Adverse Event | Placebo (n=392) | ARICEPT® (n=501)
Percent of Patients with any Adverse Event | 73 | 81
Body as a Whole
Accident | 12 | 13
Infection | 9 | 11
Headache | 3 | 4
Pain | 2 | 3
Back Pain | 2 | 3
Fever | 1 | 2
Chest Pain | <1 | 2
Cardiovascular System
Hypertension | 2 | 3
Hemorrhage | 1 | 2
Syncope | 1 | 2
Digestive System
Diarrhea | 4 | 10
Vomiting | 4 | 8
Anorexia | 4 | 8
Nausea | 2 | 6
Hemic and Lymphatic System
Ecchymosis | 2 | 5
Metabolic and Nutritional Systems
Creatine Phosphokinase Increased | 1 | 3
Dehydration | 1 | 2
Hyperlipemia | <1 | 2
Nervous System
Insomnia | 4 | 5
Hostility | 2 | 3
Nervousness | 2 | 3
Hallucinations | 1 | 3
Somnolence | 1 | 2
Dizziness | 1 | 2
Depression | 1 | 2
Confusion | 1 | 2
Emotional Lability | 1 | 2
Personality Disorder | 1 | 2
Skin And Appendages
Eczema | 2 | 3
Urogenital System
Urinary Incontinence | 1 | 2

Other Adverse Events Observed During Clinical Trials

ARICEPT® has been administered to over 600 patients with severe Alzheimer's Disease during clinical trials of at least 6 months duration, including 3 double blind placebo controlled trials, one of which had an open label extension. All adverse events occurring at least twice are included, except for those already listed in Table 4, COSTART terms too general to be informative, or events less likely to be drug caused. Events are classified by body system using the COSTART dictionary and listed using the following definitions: frequent adverse events - those occurring in at least 1/100 patients; infrequent adverse events - those occurring in 1/100 to 1/1000 patients. These adverse events are not necessarily related to ARICEPT® treatment and in most cases were observed at a similar frequency in placebo-treated patients in the controlled studies.

Body as a Whole:Frequent: abdominal pain, asthenia, fungal infection, flu syndrome; Infrequent: allergic reaction, cellulitis, malaise, sepsis, face edema, hernia.

Cardiovascular System:Frequent: hypotension, bradycardia, ECG abnormal, heart failure; Infrequent: myocardial infarction, angina pectoris, atrial fibrillation, congestive heart failure, peripheral vascular disorder, supraventricular extrasystoles, ventricular extrasystoles, cardiomegaly.

Digestive System:Frequent: constipation, gastroenteritis, fecal incontinence, dyspepsia; Infrequent: gamma glutamyl transpeptidase increase, gastritis, dysphagia, periodontitis, stomach ulcer, periodontal abscess, flatulence, liver function tests abnormal, eructation, esophagitis, rectal hemorrhage.

Endocrine System:Infrequent: diabetes mellitus.

Hemic and Lymphatic System:Frequent: anemia; Infrequent: leukocytosis.

Metabolic and Nutritional Disorders:Frequent: weight loss, peripheral edema, edema, lactic dehydrogenase increased, alkaline phosphatase increased; Infrequent hypercholesteremia, hypokalemia, hypoglycemia, weight gain, bilirubinemia, BUN increased, B12 deficiency anemia, cachexia, creatinine increased, gout, hyponatremia, hypoproteinemia, iron deficiency anemia, SGOT increased, SGPT increased.

Musculoskeletal System:Frequent: arthritis; Infrequent: arthrosis, bone fracture, arthralgia, leg cramps, osteoporosis, myalgia.

Nervous System:Frequent: agitation, anxiety, tremor, convulsion, wandering, abnormal gait; Infrequent: apathy, vertigo, delusions, abnormal dreams, cerebrovascular accident, increased salivation, ataxia, euphoria, vasodilatation, cerebral hemorrhage, cerebral infarction, cerebral ischemia, dementia, extrapyramidal syndrome, grand mal convulsion, hemiplegia, hypertonia, hypokinesia.

Respiratory System:Frequent: pharyngitis, pneumonia, cough increased, bronchitis; Infrequent: dyspnea, rhinitis, asthma.

Skin and Appendages:Frequent: rash, skin ulcer, pruritus; Infrequent: psoriasis, skin discoloration, herpes zoster, dry skin, sweating, urticaria, vesiculobullous rash

Special Senses:Infrequent: conjunctivitis, glaucoma, abnormal vision, ear pain, lacrimation disorder.

Urogenital System:Frequent: urinary tract infection, cystitis, hematuria, glycosuria; Infrequent: vaginitis, dysuria, urinary frequency, albuminuria.

Postintroduction Reports

Voluntary reports of adverse events temporally associated with ARICEPT® that have been received since market introduction that are not listed above, and that there is inadequate data to determine the causal relationship with the drug include the following: abdominal pain, agitation, cholecystitis, confusion, convulsions, hallucinations, heart block (all types), hemolytic anemia, hepatitis, hyponatremia, neuroleptic malignant syndrome, pancreatitis, and rash.

OVERDOSAGE

Because strategies for the management of overdose are continually evolving, it is advisable to contact a Poison Control Center to determine the latest recommendations for the management of an overdose of any drug.

As in any case of overdose, general supportive measures should be utilized. Overdosage with cholinesterase inhibitors can result in cholinergic crisis characterized by severe nausea, vomiting, salivation, sweating, bradycardia, hypotension, respiratory depression, collapse and convulsions. Increasing muscle weakness is a possibility and may result in death if respiratory muscles are involved. Tertiary anticholinergics such as atropine may be used as an antidote for ARICEPT® overdosage. Intravenous atropine sulfate titrated to effect is recommended: an initial dose of 1.0 to 2.0 mg IV with subsequent doses based upon clinical response. Atypical responses in blood pressure and heart rate have been reported with other cholinomimetics when co-administered with quaternary anticholinergics such as glycopyrrolate. It is not known whether ARICEPT® and/or its metabolites can be removed by dialysis (hemodialysis, peritoneal dialysis, or hemofiltration).

Dose-related signs of toxicity in animals included reduced spontaneous movement, prone position, staggering gait, lacrimation, clonic convulsions, depressed respiration, salivation, miosis, tremors, fasciculation and lower body surface temperature.

DOSAGE AND ADMINISTRATION

The dosages of ARICEPT® shown to be effective in controlled clinical trials are 5 mg and 10 mg administered once per day.

The higher dose of 10 mg did not provide a statistically significantly greater clinical benefit than 5 mg. There is a suggestion, however, based upon order of group mean scores and dose trend analyses of data from these clinical trials, that a daily dose of 10 mg of ARICEPT® might provide additional benefit for some patients. Accordingly, whether or not to employ a dose of 10 mg is a matter of prescriber and patient preference.

Evidence from the controlled trials indicates that the 10 mg dose, with a one week titration, is likely to be associated with a higher incidence of cholinergic adverse events than the 5 mg dose. In open label trials using a 6 week titration, the frequency of these same adverse events was similar between the 5 mg and 10 mg dose groups. Therefore, because steady state is not achieved for 15 days and because the incidence of untoward effects may be influenced by the rate of dose escalation, treatment with a dose of 10 mg should not be contemplated until patients have been on a daily dose of 5 mg for 4 to 6 weeks.

Each teaspoon (5 mL) of ARICEPT® Oral Solution contains a 5 mg dose. Patients should be instructed as to how to measure their dose of ARICEPT® Oral Solution in teaspoons.

ARICEPT® Oral Solution should be taken in the evening, just prior to retiring.

ARICEPT® Oral Solution can be taken with or without food.

HOW SUPPLIED

ARICEPT® Oral Solution is a clear, colorless to light yellow solution containing 1 mg of donepezil hydrochloride in each mL (1 mg/mL). Each teaspoon (5mL) contains 5 mg of donepezil hydrochloride.

NDC#62856-851-30 300 mL HDPE Bottles

Storage: Store at controlled room temperature, 15°C to 30°C (59°F to 86°F).

RX only

ARICEPT® is a registered trademark of Eisai Co., Ltd.

Manufactured and Marketed by Eisai Inc., Teaneck, NJ 07666

Marketed by

Pfizer Inc, New York, NY 10017

© 2006 Eisai Inc.

Printed in U.S.A.

Revised October 2006